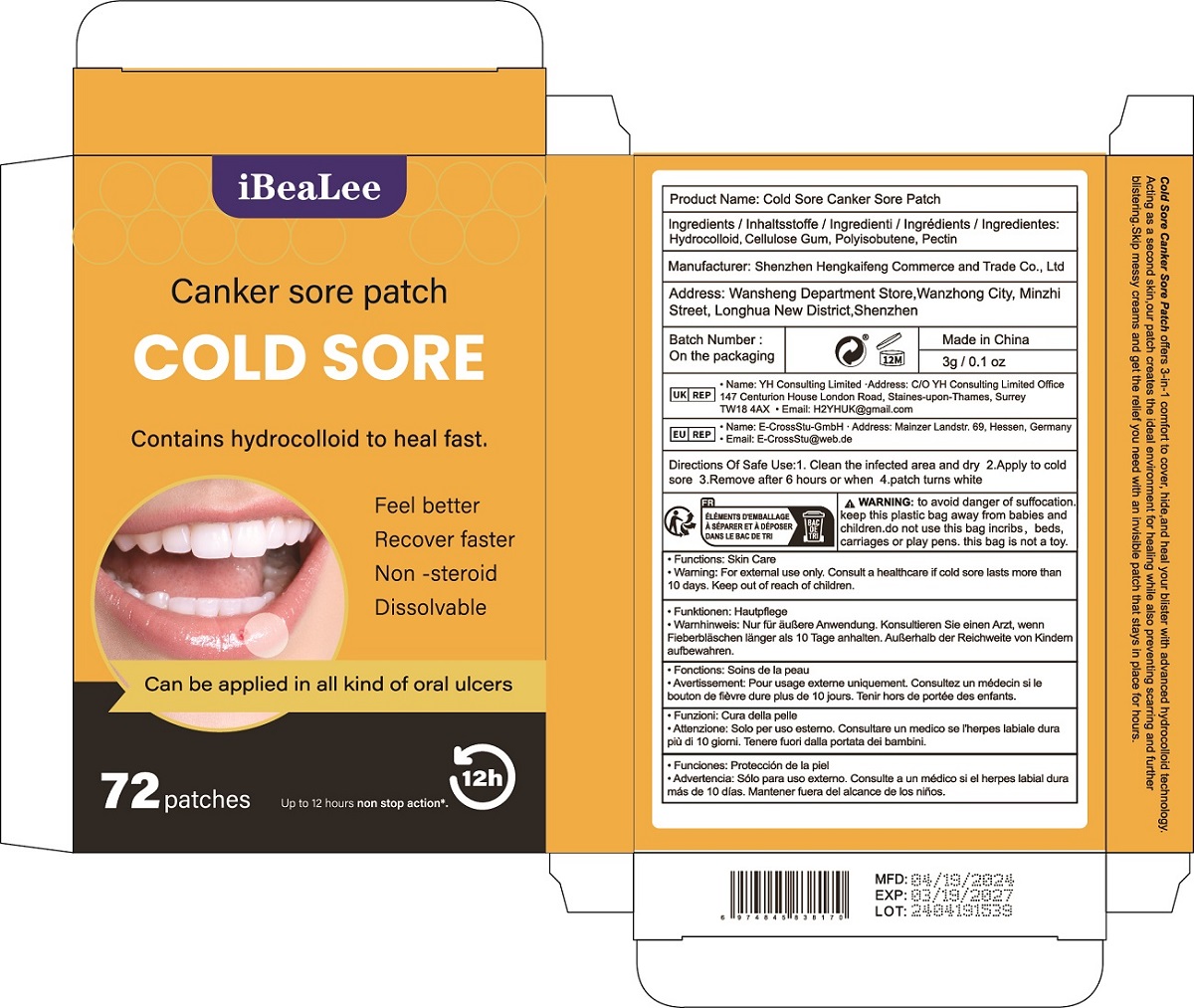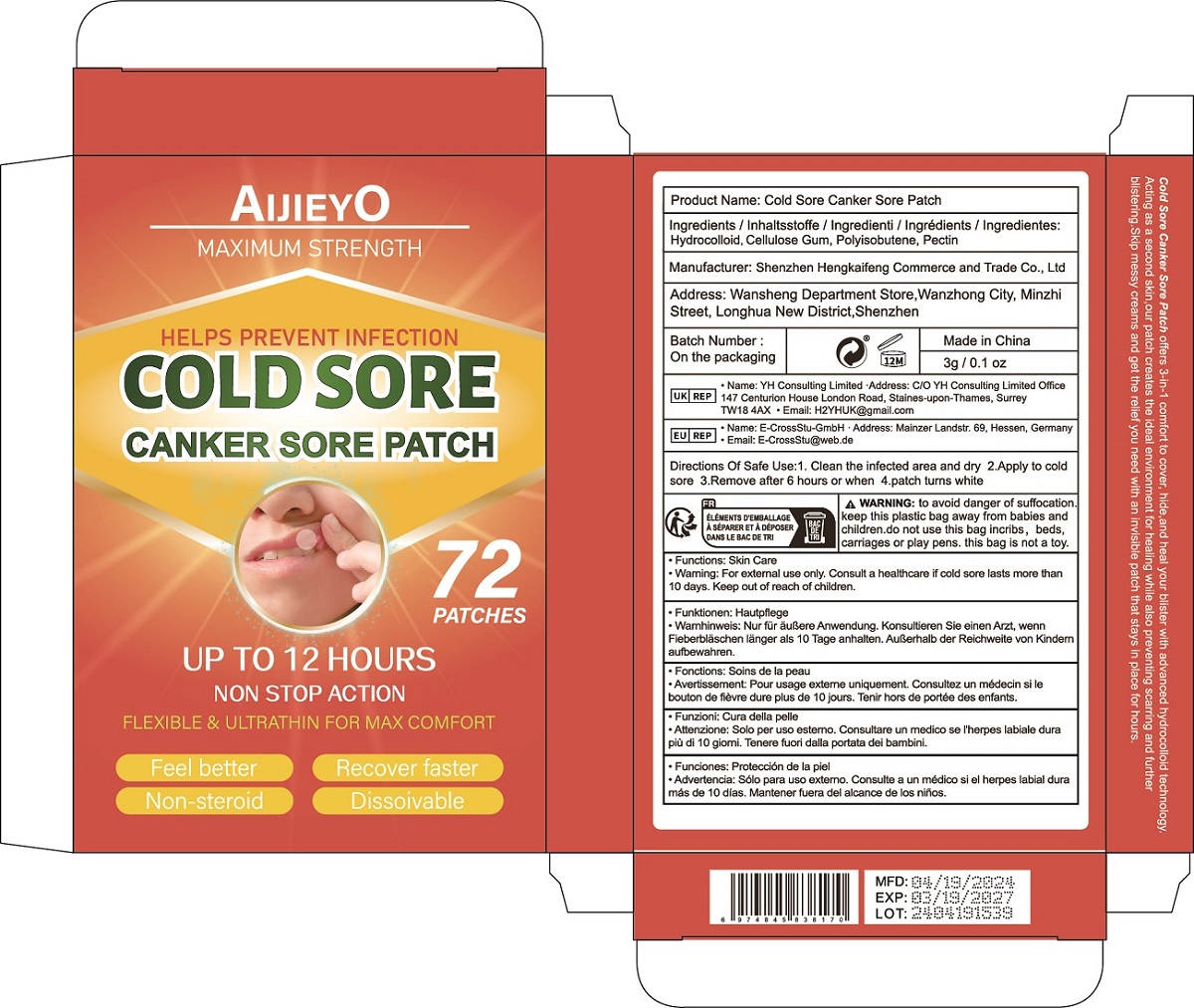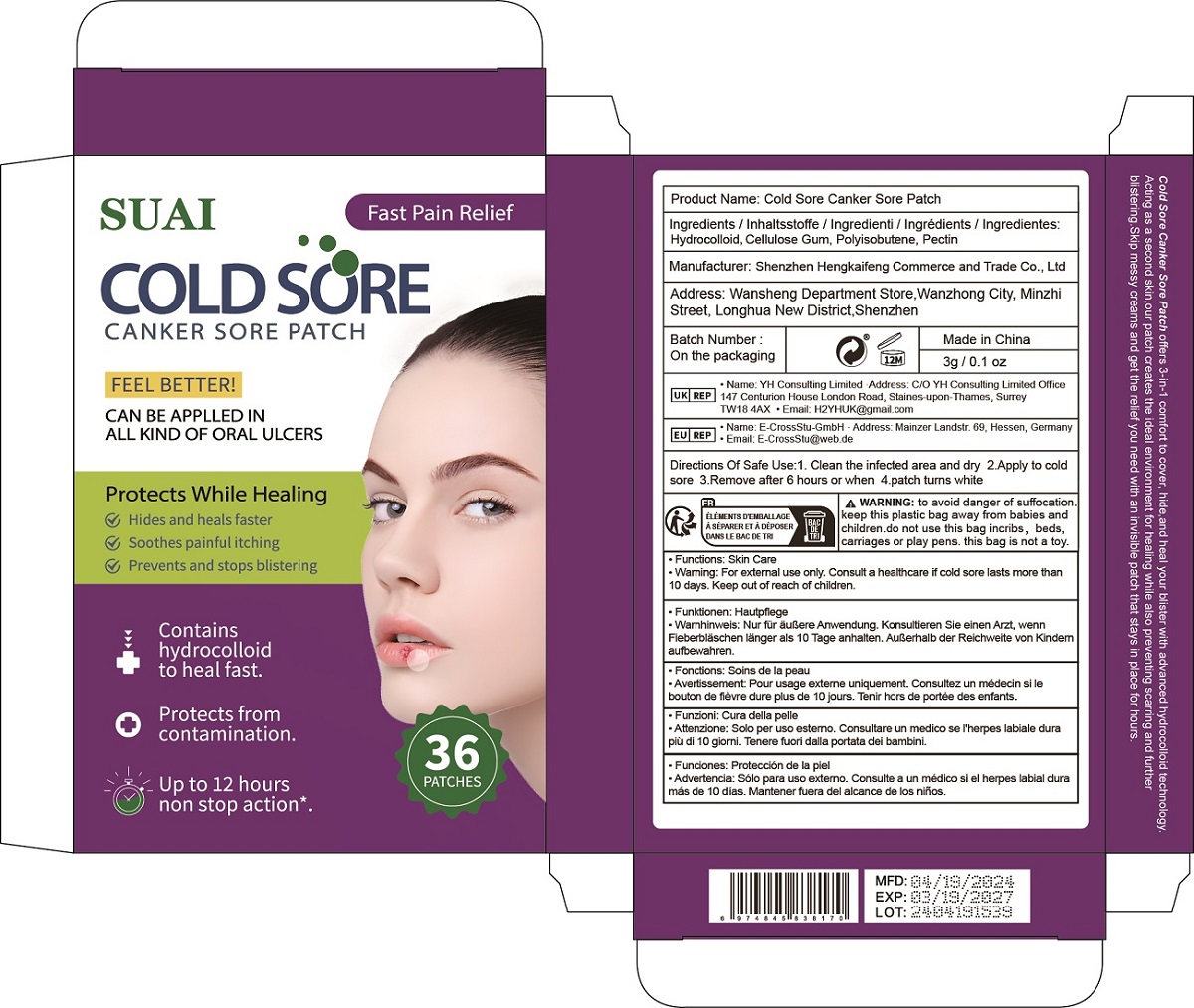 DRUG LABEL: Cold Sore Canker Sore Patch
NDC: 84117-008 | Form: PATCH
Manufacturer: Shenzhen Hengkaifeng Commerce and Trade Co., Ltd
Category: otc | Type: HUMAN OTC DRUG LABEL
Date: 20240502

ACTIVE INGREDIENTS: PECTIN 5 g/100 g
INACTIVE INGREDIENTS: HYDROGENATED POLYISOBUTENE (450 MW); CARBOXYMETHYLCELLULOSE SODIUM

ACTIVE INGREDIENT

Pectin 5%

Purpose

Canker Sore Treatment

Use

Cold Sore Canker Sore Patch offers 3-in-1 comfort to cover, hide,and heal your blister with advanced hydrocolloid technology.
Acting as a second skin,our patch creates the ideal environment for healing while also preventing scarring and further
blistering.Skip messy creams and get the relief you need with an invisible patch that stays in place for hours.

Warnings

For external use only. Consult a healthcare if cold sore lasts more than
10 days. Keep out of reach of children.

Keep Out Of Reach Of Children

Directions Of Safe Use:

1. Clean the infected area and dry

2.Apply to cold sore

3.Remove after 6 hours or when

4.patch turns white

Inactive ingredients

Hydrocolloid, Cellulose Gum, Polyisobutene